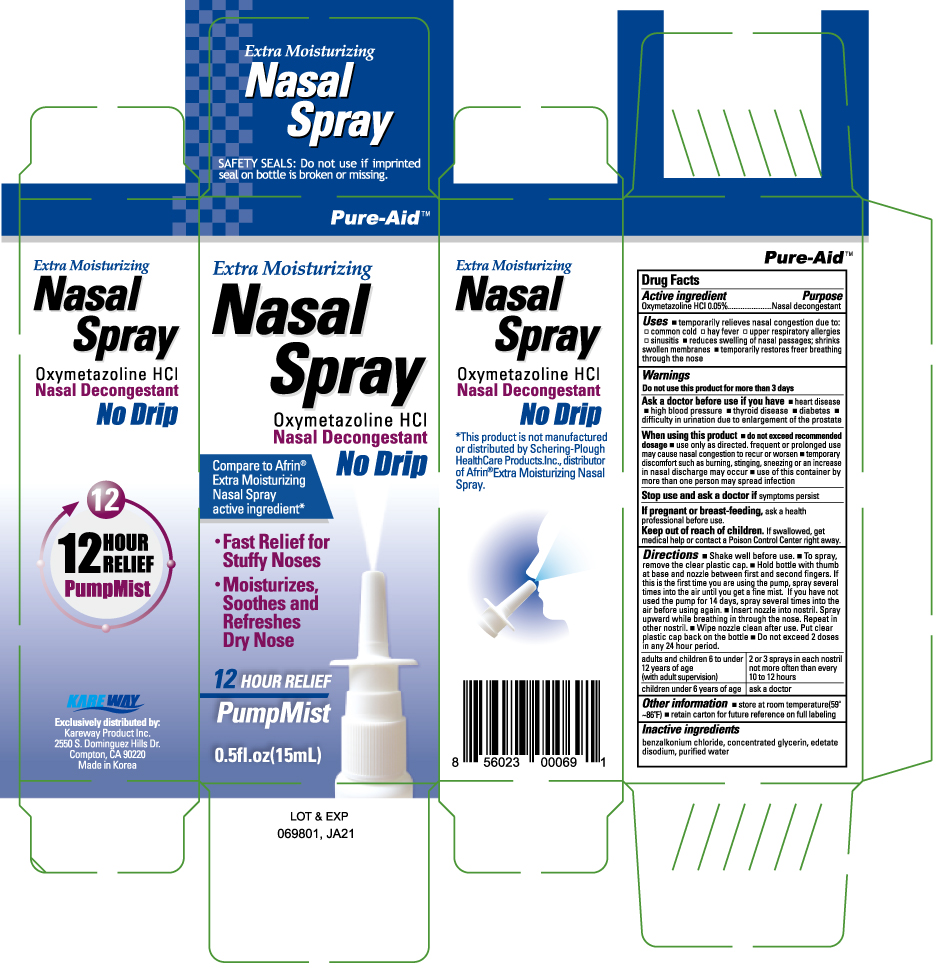 DRUG LABEL: Nasal Decongestant Extra Moisturizing
NDC: 67510-0069 | Form: SPRAY
Manufacturer: Kareway Product, Inc.
Category: otc | Type: HUMAN OTC DRUG LABEL
Date: 20210915

ACTIVE INGREDIENTS: OXYMETAZOLINE HYDROCHLORIDE 0.05 g/100 mL
INACTIVE INGREDIENTS: BENZALKONIUM CHLORIDE; EDETATE DISODIUM; GLYCERIN; WATER

Pure-Aid Nasal Spray Extra-Moisturizing

Active ingredient

Oxymetazoline HCl 0.05%

Purpose

Nasal decongestant

Uses

- temporarily relieves nasal congestion due to:

- common cold
- hay fever
- upper respiratory allergies
- sinusitis

- reduces swelling of nasal passages; shrinks swollen membranes
- temporarily restores freer breathing through the nose

Warnings

Do not use this product for more than 3 days

Ask a doctor before use if you have

- heart disease
- high blood pressure
- thyroid disease
- diabetes
- difficulty in urination due to enlargement of the prostate

When using this product

- do not exceed recommended dosage
- use only as directed. frequent of prolonged use may cause nasal congestion to recur or worsen
- temporary discomfort such as burning, stinging, or an increase in nasal discharge may occur
- use of this container by more than one person may spread infection

Stop use and ask a doctor if

symptoms persist

If pregnant or breast-feeding,

ask a health professional before use.

Keep out of reach of children.

If swallowed, get medical help or contact a Poison Control Center right away.

Directions

- Shake well before use.
- To spray, remove the clear plastic cap.
- Hold bottle with thumb at base and nozzle between first and second fingers. If this is the first time you are using the pump, spray several times into the air until you get a fine mist. If you have not used the pump for 14 days, spray several times into the air before using again.
- Insert nozzle into nostril. Spray upward while breathing in through the nose. Repeat in other nostril.
- Wipe nozzle clean after use. Put clear plastic cap back on the bottle
- Do not exceed 2 doses in any 24 hour period.

adults and children 6 to under 12 years of age (with adult supervision) | 2 or 3 spray in each nostril not more often than every 10 to 12 hours
children under 6 years of age | ask a doctor

Other information

- store at room temperature(59°~86°F)

- retain carton for future reference on full labeling

Inactive ingredients

benzalkonium chloride, concentrated glycerin, edetate disodium, purified water

Carton image

Nasal Spray Extra Moisturizing